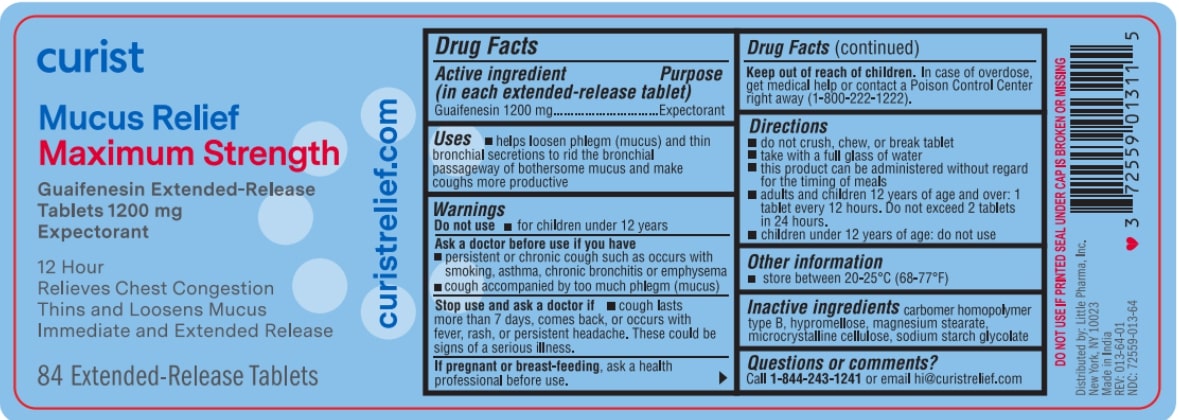 DRUG LABEL: Curist Mucus Relief
NDC: 72559-013 | Form: TABLET, EXTENDED RELEASE
Manufacturer: Little Pharma, Inc.
Category: otc | Type: HUMAN OTC DRUG LABEL
Date: 20251028

ACTIVE INGREDIENTS: GUAIFENESIN 1200 mg/1 1
INACTIVE INGREDIENTS: SODIUM STARCH GLYCOLATE TYPE A POTATO; CARBOMER HOMOPOLYMER TYPE B (ALLYL PENTAERYTHRITOL OR ALLYL SUCROSE CROSSLINKED); HYPROMELLOSE, UNSPECIFIED; MAGNESIUM STEARATE; MICROCRYSTALLINE CELLULOSE

Curist Mucus Relief Max Str (Guaifenesin 1200 mg) ER

KEEP THE CARTON. IT CONTAINS IMPORTANT INFORMATION

Drug Facts

Active ingredient (in each extended-release tablet)

Guaifenesin 1200 mg

Purpose

Expectorant

Uses

- helps loosen phlegm (mucus) and thin bronchial secretions to rid the bronchial passageways of bothersome mucus and make coughs more productive

Warnings

Do not use

- for children under 12 years of age

Ask a doctor before use if you have

- persistent or chronic cough such as occurs with smoking, asthma, chronic bronchitis, or emphysema
- cough accompanied by too much phlegm (mucus)

Stop use and ask a doctor if

- cough lasts more than 7 days, comes back, or occurs with fever, rash, or persistent headache. These could be signs of a serious illness.

PREGNANCY OR BREAST FEEDING

If pregnant or breast-feeding, ask a health professional before use.

Keep out of reach of children. In case of overdose, get medical help or contact a Poison Control Center right away (1-800-222-1222).

Directions

- do not crush, chew, or break tablet
- take with a full glass of water
- this product can be administered without regard for the timing of meals
- adults and children 12 years of age and over: 1 tablet every 12 hours. Do not exceed 2 tablets in 24 hours.
- children under 12 years of age: do not use

Other information

- Tamper evident: do not use if carton is open or if printed seal on blister is broken or missing.
- store between 20°-25°C (68°-77°F)

INACTIVE INGREDIENT

Inactive ingredients carbomer homopolymer type B, hypromellose, magnesium stearate, microcrystalline cellulose, sodium starch glycolate

Questions?

Contact 1-877-770-3183

Mon-Fri 8:00 AM EST to 5:00 PM PST.

Distributed by:
Little Pharma, Inc.

New York, NY 10023

Made in India

PACKAGE LABEL

curist

Mucus Relief Maximum Strength

Guaifenesin Extended-Release Tablets 1200 mg

Expectorant

12 Hour

Relieves Chest Congestion

Thins and Loosens Mucus

Immediate and Extended Release

84 Extended-Release Tablets